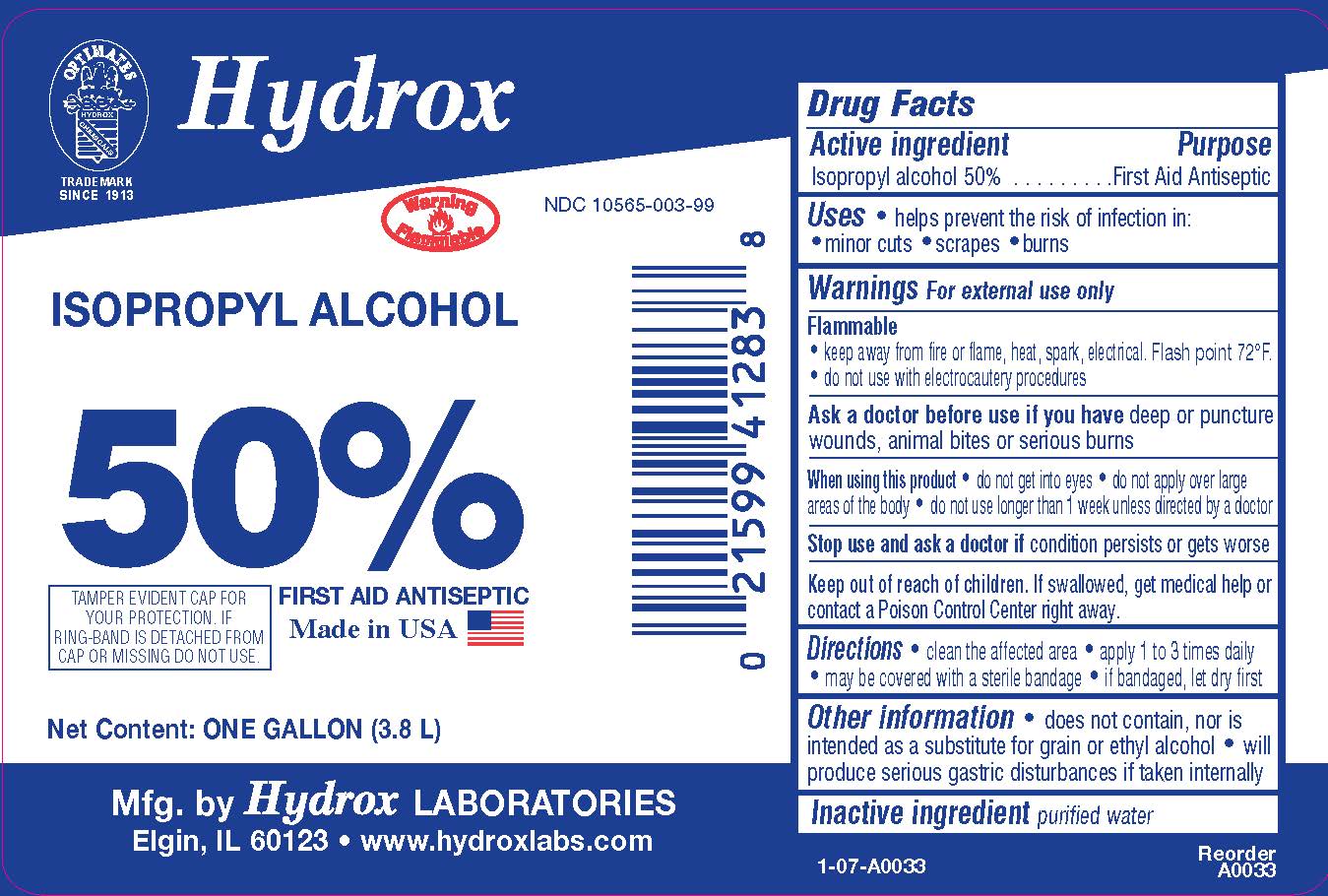 DRUG LABEL: Isopropyl Alcohol 50%
NDC: 10565-003 | Form: SOLUTION
Manufacturer: Hydrox Laboratories
Category: otc | Type: HUMAN OTC DRUG LABEL
Date: 20260112

ACTIVE INGREDIENTS: ISOPROPYL ALCOHOL 50 mL/100 mL
INACTIVE INGREDIENTS: WATER

Isopropyl Rubbing Alcohol 50%

Drug Facts

Active Ingredient

Isopropyl Alcohol 50%

Purpose:

First Aid Antiseptic

INDICATIONS AND USAGE

Usesfirst aid to help prevent the risk of infection in: minor cuts, scrapes, burns.

Warnings For external use only

Flammable

- Keep away from fire or flame, heat, spark, electrical. Flash point 72°F.
- do not use with eletocautery procedures.

Ask a doctor before use if you have deep or puncture wounds, animal bites or serious burns.

When using this product

- do not get into eyes
- do not apply over large areas of the body
- do not use longer than 1 week unless directed by a doctor

Stop use and ask a doctor if condition persists or gets worse

Keep out of reach of children. If swallowed, get medical help or contact a Poison Control Center right away.

DOSAGE AND ADMINISTRATION

<Directions clean the affected area. apply 1 to 3 times daily.

Other information does not contain, nor is intended as a substitue for grain or ethyl alcohol. will produce serious gastric disturbances if taken internally.

Inactive Ingredient purified water

Principal Display Panel

Hydrox

Isopropyl Rubbing Alcohol

A cooling and refreshing and massaging compound

50%

First Aid Antiseptic

TAMPER EVIDENT CAP FOR YOUR PROTECTION. IF RING-BAND IS DETACHED FROM CAP OR MISSING, DO NOT USE.

WARNING: FLAMMABLE!

Hydrox Laboratories

Elgin, IL 60123